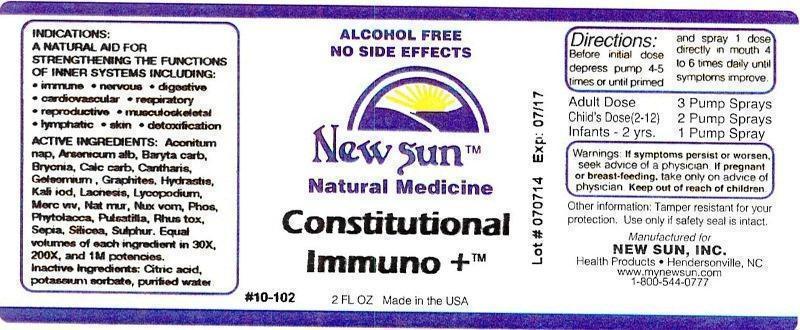 DRUG LABEL: Constitutional Immuno
NDC: 66579-0064 | Form: LIQUID
Manufacturer: New Sun Inc.
Category: homeopathic | Type: HUMAN OTC DRUG LABEL
Date: 20140801

ACTIVE INGREDIENTS: ACONITUM NAPELLUS 30 [hp_X]/59 mL; ARSENIC TRIOXIDE 30 [hp_X]/59 mL; BARIUM CARBONATE 30 [hp_X]/59 mL; BRYONIA ALBA ROOT 30 [hp_X]/59 mL; OYSTER SHELL CALCIUM CARBONATE, CRUDE 30 [hp_X]/59 mL; LYTTA VESICATORIA 30 [hp_X]/59 mL; GELSEMIUM SEMPERVIRENS ROOT 30 [hp_X]/59 mL; GRAPHITE 30 [hp_X]/59 mL; GOLDENSEAL 30 [hp_X]/59 mL; POTASSIUM CARBONATE 30 [hp_X]/59 mL; LACHESIS MUTA VENOM 30 [hp_X]/59 mL; LYCOPODIUM CLAVATUM SPORE 30 [hp_X]/59 mL; MERCURY 30 [hp_X]/59 mL; SODIUM CHLORIDE 30 [hp_X]/59 mL; STRYCHNOS NUX-VOMICA SEED 30 [hp_X]/59 mL; PHOSPHORUS 30 [hp_X]/59 mL; PHYTOLACCA AMERICANA ROOT 30 [hp_X]/59 mL; PULSATILLA VULGARIS 30 [hp_X]/59 mL; TOXICODENDRON PUBESCENS LEAF 30 [hp_X]/59 mL; SEPIA OFFICINALIS JUICE 30 [hp_X]/59 mL; SILICON DIOXIDE 30 [hp_X]/59 mL; SULFUR 30 [hp_X]/59 mL
INACTIVE INGREDIENTS: CITRIC ACID MONOHYDRATE; POTASSIUM SORBATE; WATER

Constitutional Immuno +

DOSAGE AND ADMINISTRATION

Directions: Before initial dose depress pump 4-5 times or until primed and spray 1 dose directly in mouth 4 to 6 times daily until symptoms improve.

Adult Dose: 3 Pump Sprays

Child's Dose (2-12): 2 Pump Sprays

Infants - 2 yrs: 1 Pump Spray

WARNINGS

Warnings: If symptoms persist or worsen, seek advice of physician. If pregnant or breast-feeding, take only on advice of physician.

Keep out of reach of children.

Other information: Tamper resistant for your protection. Use only if safety seal is intact.

PURPOSE

Indications: A NATURAL AID FOR STRENGTHENING THE FUNCTIONS OF INNER SYSTEMS INCLUDING: •immune •nervous •digestive •cardiovascular •respiratory •reproductive •musculoskeletal •lymphatic •skin •detoxification

ACTIVE INGREDIENT

Active Ingredients: Aconitum napellus, Arsenicum album, Baryta carbonica, Bryonia, Calcarea carbonica, Cantharis, Gelsemium sempervirens, Graphites, Hydrastis canadensis, Kali carbonicum, Lachesis mutus, Lycopodium clavatum, Mercurius vivus, Natrum muriaticum, Nux vomica, Phosphorus, Phytolacca decandra, Pulsatilla, Rhus toxicodendron, Sepia, Silicea, Sulphur. Equal volumes of each ingredient in 30X, 200X, and 1M potencies.

Inactive Ingredient: Citric acid, potassium sorbate, purified water.

INDICATIONS AND USAGE

Indications: A NATURAL AID FOR STRENGTHENING THE FUNCTIONS OF INNER SYSTEMS INCLUDING:

- immune
- nervous
- digestive
- cardiovascular
- respiratory
- reproductive
- musculoskeletal
- lymphatic
- skin
- detoxification